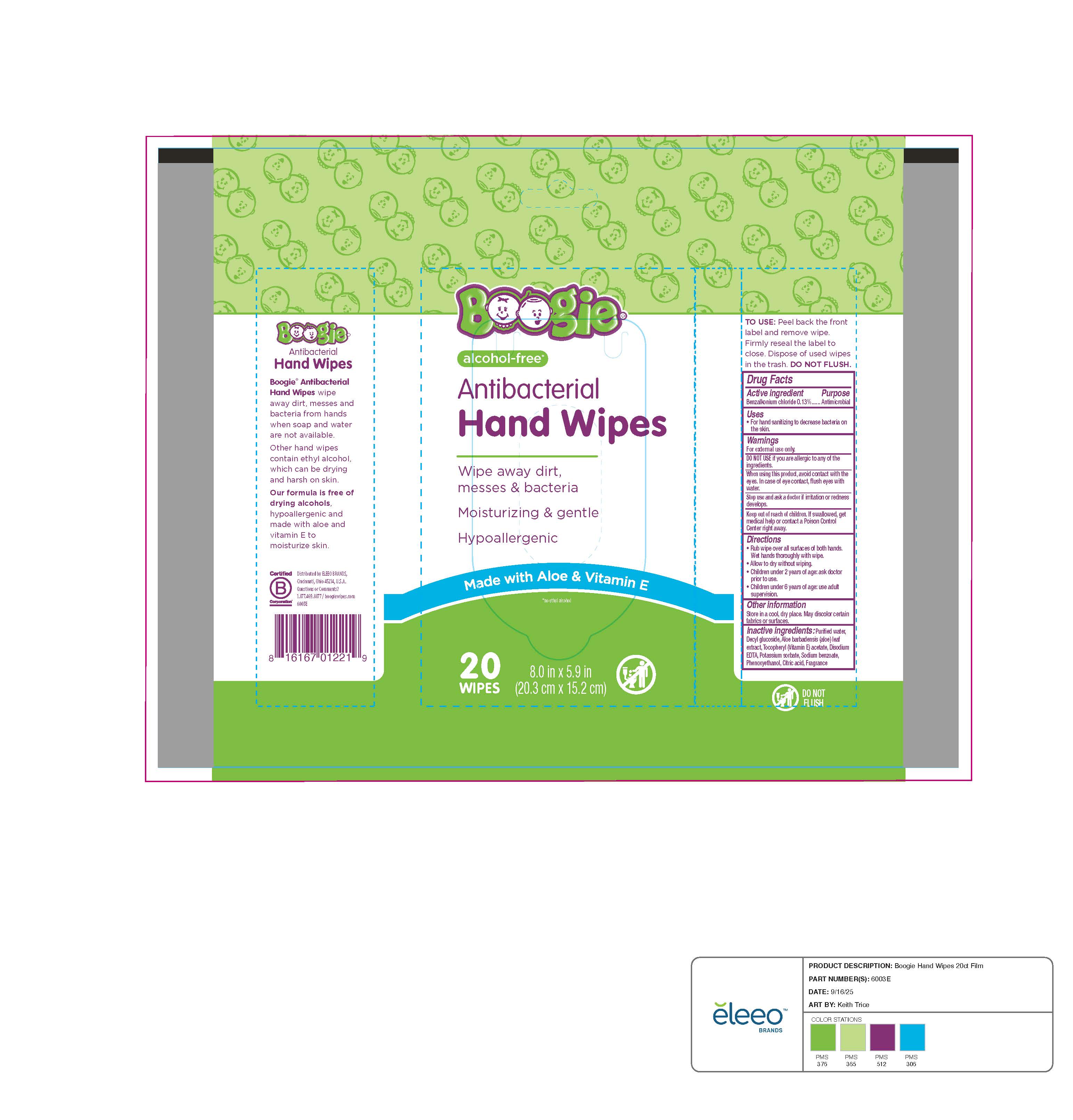 DRUG LABEL: Boogie Hands Antibacterial Wet Wipes
NDC: 79747-014 | Form: CLOTH
Manufacturer: ELEEO BRANDS LLC
Category: otc | Type: HUMAN OTC DRUG LABEL
Date: 20250930

ACTIVE INGREDIENTS: BENZALKONIUM CHLORIDE 0.0013 g/100 mL
INACTIVE INGREDIENTS: .ALPHA.-TOCOPHEROL ACETATE; WATER; DECYL GLUCOSIDE; POTASSIUM SORBATE; SODIUM BENZOATE; ALOE VERA LEAF; PHENOXYETHANOL; EDETATE DISODIUM; CITRIC ACID

Boogie Hands Antibacterial Hand Wipes

Active ingredients

Benalkonium chloride (0.13%)

Purpose

Antimicrobial

Use

For hand sanitizing to decrease bacteria on skin

Warnings

For external use only

Do Not Use

if you are allergic to any of the ingredients

When using this product

avoid contact with the eyes. In case of eye contact, flush eyes with water.

Stop use and ask a doctor if

if irritation or redness develops.

Keep out of reach of children.

If swallowed, get medical help or contact a Poison Control Center right away

Directions:

- Rub wipe over all surfaces of both hands. Wet hands thoroughly with wipe.

- Allow to dry without wiping.

- Children under 2 years of age:ask doctor prior to use.

- Children under 6 years of age:use adult supervision.

Inactive ingredients

Purified water, Decyl glucoside, Aloe barbadensis(aloe) leaf extract, Tocopheryl (Vitamin E) acetate, Disodium EDTA, Potassium sorbate, Sodium benzoate, Phenoxyethanol, Citric acid, Fragrance

PRINCIPAL DISPLAY PANEL

20ct NDC:79747-014-02